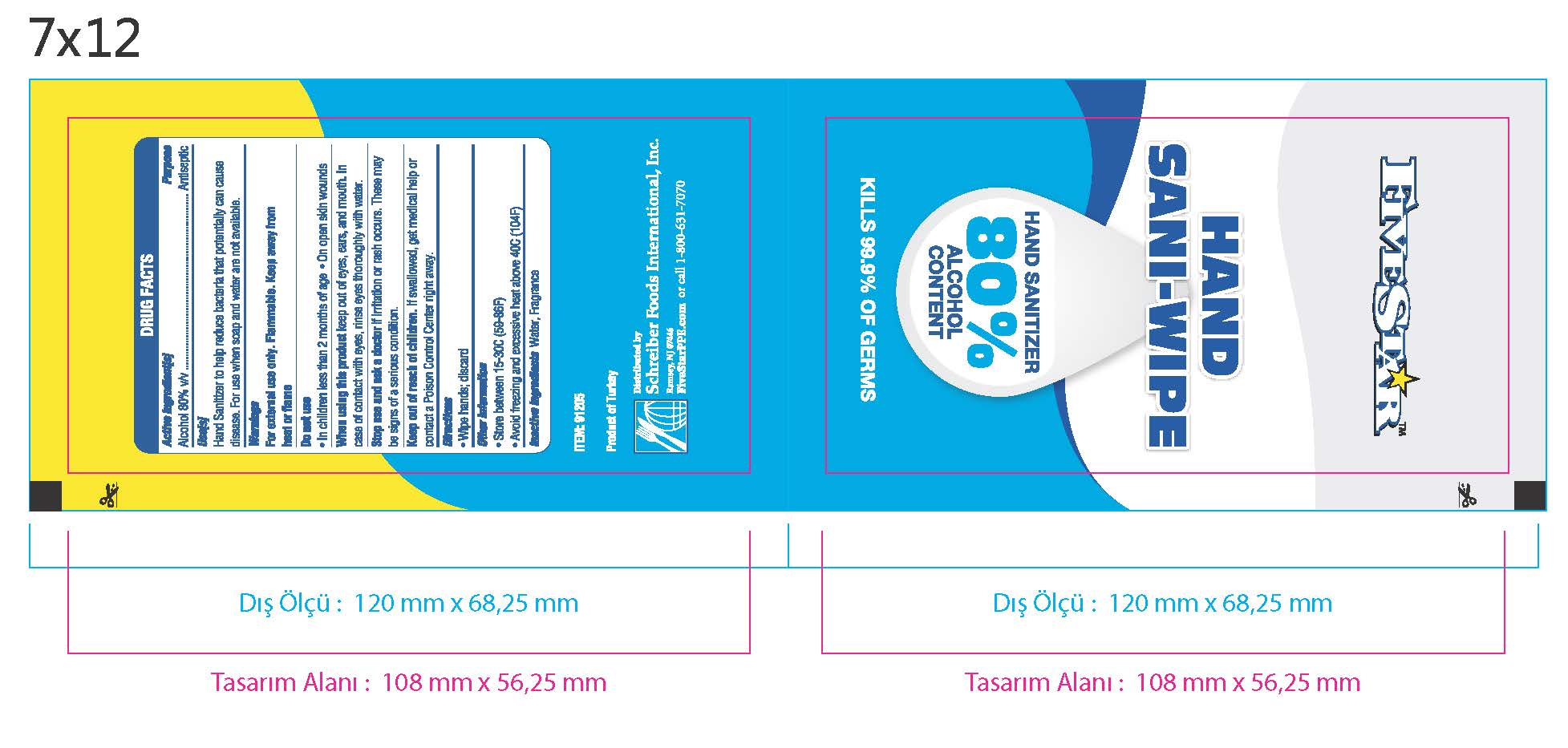 DRUG LABEL: Hand Wipes
NDC: 76758-912 | Form: CLOTH
Manufacturer: Schreiber Foods International, Inc.
Category: otc | Type: HUMAN OTC DRUG LABEL
Date: 20200604

ACTIVE INGREDIENTS: ALCOHOL 80 mL/100 mL
INACTIVE INGREDIENTS: WATER

Antiseptic Alcohol Wipes

Active ingredient

Alcohol 80% v/v

Purpose

Antiseptic

Uses

Hand Sanitizer to help reduce bacteria that potentially can cause disease. For use when soap and water are not available.

Warnings

For external use only. Flammable. Keep away from heat or flame.

Do not use

- In children less than 2 months of age
- On open skin wounds

When using this product

keep out of eyes, ears, and mouth. Incase of contact with eyes, rinse eyes thoroughly with water.

Stop use and ask a doctor

if irritation or rash occurs. These may be signs of a serious condition.

Keep out of reach of children. If swalled, get medical help or contact a PoisonControl Center right away.

Directions

- Wipe hands;discard

Other Instructions

- Store between 15-30C (59-86F)
- Avoid freezing and excessive heat above 40C (104F)

Inactive Ingredients

Water, Fragrance

FIVESTAR (TM)

HAND SANI-WIPE

HAND SANITIZER 80& ALCOHOL CONTENT

KILLS 99.9% OF GERMS

ITEM: 91205

Product of Turkey

Distributed by: Schreiber Foods International, Inc. Ramsey NJ 07466

FiveStarPPE.com or call 1-800-631-7070